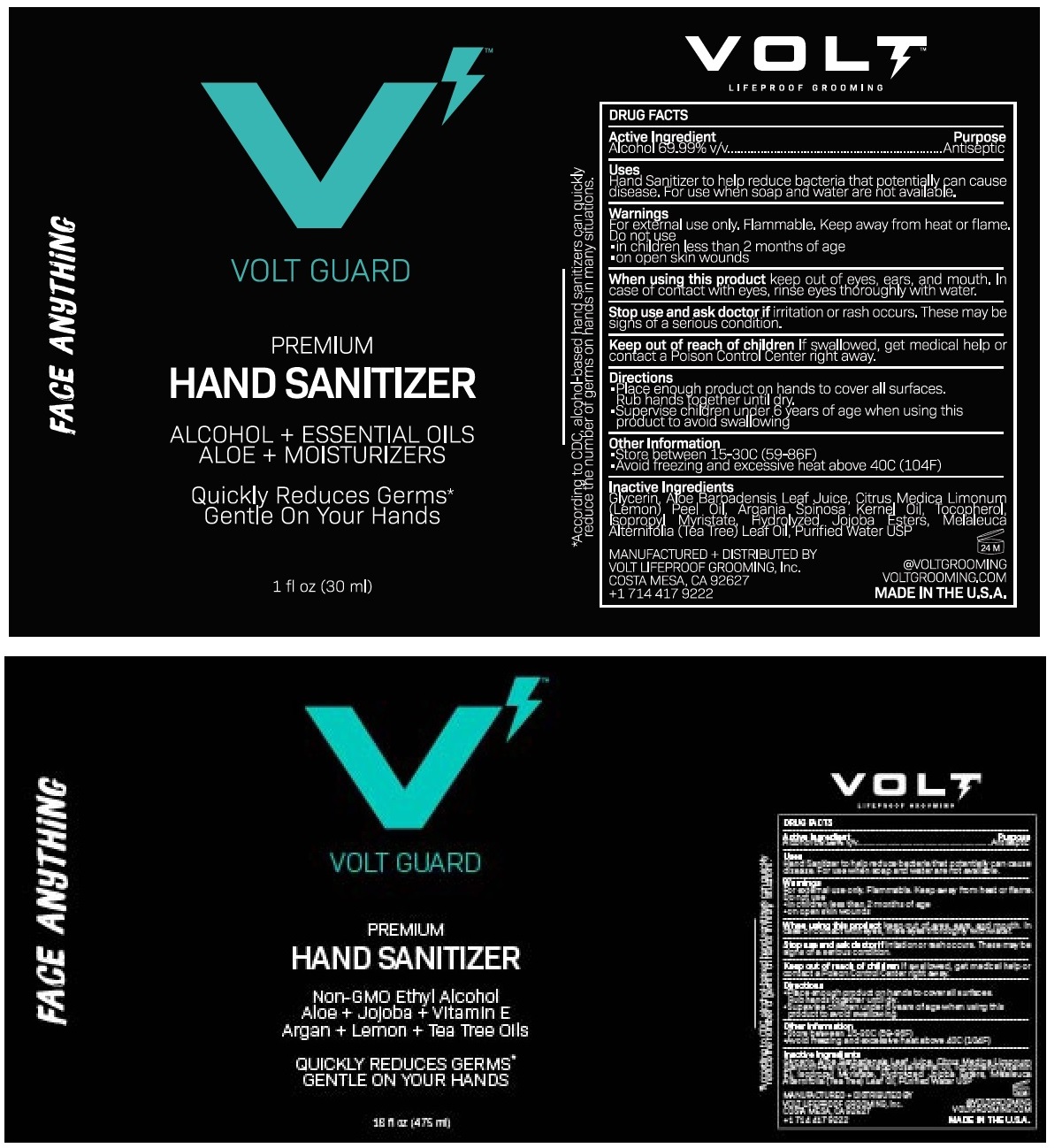 DRUG LABEL: VOLT Guard Hand Sanitizer
NDC: 73868-001 | Form: SPRAY
Manufacturer: Volt Lifeproof Grooming, Inc.
Category: otc | Type: HUMAN OTC DRUG LABEL
Date: 20200513

ACTIVE INGREDIENTS: ALCOHOL 69.99 mL/100 mL
INACTIVE INGREDIENTS: GLYCERIN; ALOE VERA LEAF; LEMON OIL; ARGAN OIL; TOCOPHEROL; ISOPROPYL MYRISTATE; HYDROLYZED JOJOBA ESTERS (ACID FORM); TEA TREE OIL; WATER

VOLT Guard Hand Sanitizer

Active Ingredient

Alcohol 69.99% v/v

Purpose

Antiseptic

Uses

Hand Sanitizer to help reduce bacteria that potentially can cause disease. For use when soap and water are not available.

Warnings

For external use only. Flammable. Keep away from heat or flame.

Do not use

- in children less than 2 months of age
- on open skin wounds

When using this product keep out of eyes, ears, and mouth. In case of contact with eyes, rinse eyes thoroughly with water.

Stop use and ask doctor if irritation or rash occurs. These may be signs of a serious condition.

Keep out of reach of children If swallowed, get medical help or contact a Poison Control Center right away.

Directions

- Place enough product on hands to cover all surfaces. Rub hands together until dry.
- Supervise children under 6 years of age when using this product to avoid swallowing

Other Information

- Store between 15-30C (59-86F)
- Avoid freezing and excessive heat above 40C (104F)

Inactive Ingredients

Glycerin, Aloe Barbadensis Leaf Juice, Citrus Medica limonum (Lemon) Peel Oil, Argania Spinosa Kernel Oil, Tocopherol, Isopropyl Myristate, Hydrolyzed Jojoba Esters, Melaleuca Alternifolia (Tea Tree) Leaf Oil, Purified Water USP

PREMIUM

ALCOHOL + ESSENTIAL OILS

ALOE + MOISTURIZERS

Quickly Reduces Germs*

Gentle On Your Hands

FACE ANYTHING

*According to CDC, alcohol-based hand sanitizers can quickly reduce the number of germs on hands in many situations.

MANUFACTURED + DISTRIBUTED BY

VOLT LIFEPROOF GROOMING, Inc.

COSTA MESA, CA 92627

+1 714 417 9222

@VOLTGROOMING

VOLTGROOMING.COM

MADE IN THE U.S.A.